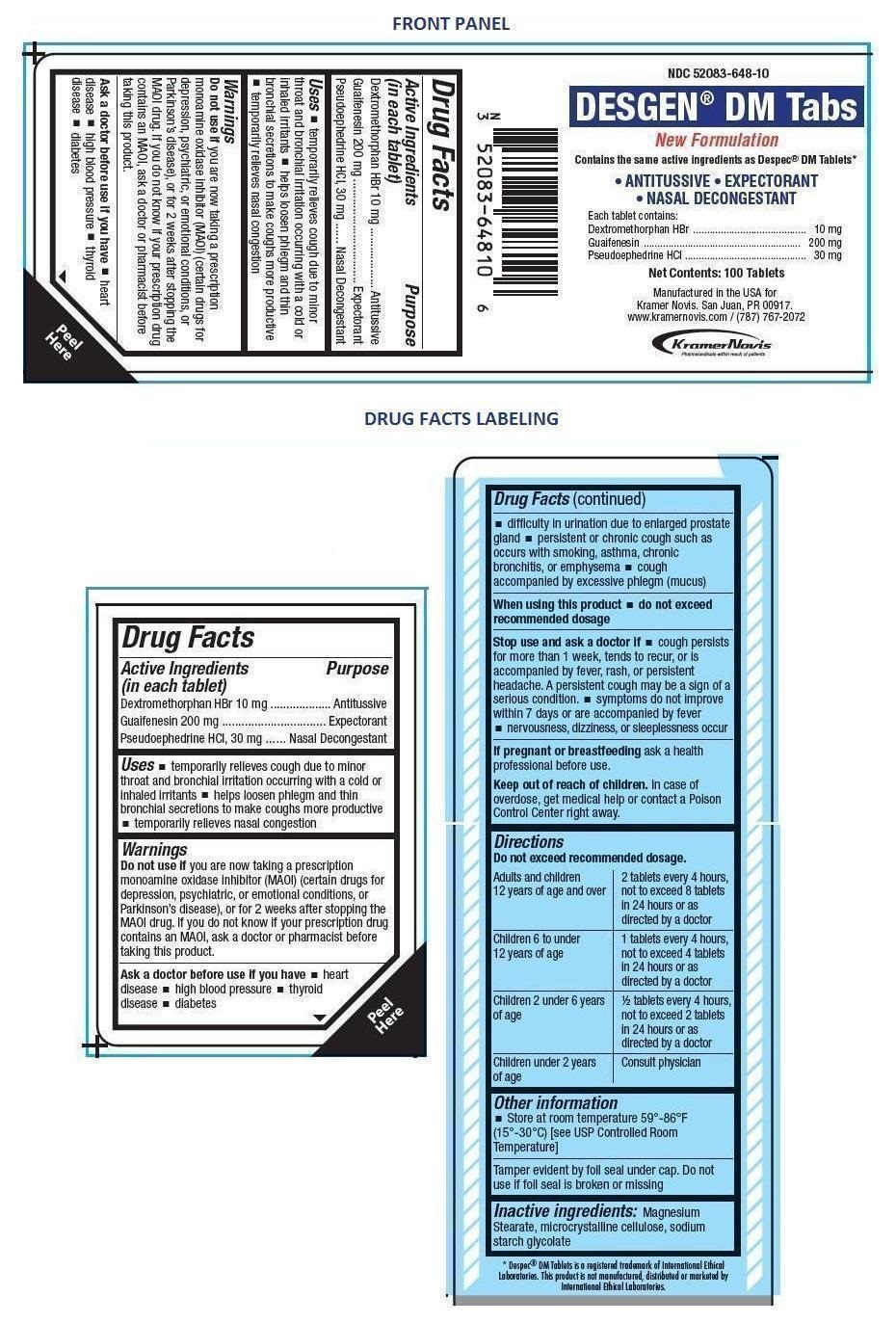 DRUG LABEL: DESGEN DM Tabs
NDC: 52083-648 | Form: TABLET
Manufacturer: KRAMER NOVIS
Category: otc | Type: HUMAN OTC DRUG LABEL
Date: 20240104

ACTIVE INGREDIENTS: DEXTROMETHORPHAN HYDROBROMIDE 10 mg/1 1; GUAIFENESIN 200 mg/1 1; PSEUDOEPHEDRINE HYDROCHLORIDE 30 mg/1 1
INACTIVE INGREDIENTS: MAGNESIUM STEARATE; MICROCRYSTALLINE CELLULOSE; SODIUM STARCH GLYCOLATE TYPE A POTATO

DESGEN DM Tabs

Active ingredients (in each tablet)

Dextromethorphan HBr 10 mg

Guaifenesin 200 mg

Pseudoephedrine HCl, 30 mg

Purpose

Antitussive

Expectorant

Nasal Decongestant

Keep out of reach of children. In case of overdose, get medical help or contact a Poison Control Center right away.

INDICATIONS AND USAGE

Uses • temporarily relieves cough due to minor throat and bronchial irritation occurring with a cold or inhaled irritants • helps loosen phlegm and thin bronchial secretions to make coughs more productive • temporarily relieves nasal congestion

Warnings

Do not use if you are now taking a prescription monoamine oxidase inhibitor (MAOI) (certain drugs for depression, psychiatric, or emotional conditions, or Parkinson’s disease), or for 2 weeks after stopping the MAOI drug. If you do not know if your prescription drug contains an MAOI, ask a doctor or pharmacist before taking this product.

Ask a doctor before use if you have • heart disease • high blood pressure • thyroid disease • diabetes • difficulty in urination due to enlarged prostate gland • persistent or chronic cough such as occurs with smoking, asthma, chronic bronchitis, or emphysema • cough accompanied by excessive phlegm (mucus)

When using this product • do not exceed recommended dosage

Stop use and ask a doctor if • cough persists for more than 1 week, tends to recur, or is accompanied by fever, rash, or persistent headache. A persistent cough may be a sign of a serious condition • symptoms do not improve within 7 days or are accompanied by fever • nervousness, dizziness, or sleeplessness occur

If pregnant or breastfeeding ask a health professional before use.

Directions

Do not exceed recommended dosage.

Adults and children; 12 years of age and over | 2 tablets every 4 hours,; not to exceed 8 tablets; in 24 hours or as; directed by a doctor
Children 6 to under; 12 years of age | 1 tablets every 4 hours,; not to exceed 4 tablets; in 24 hours or as; directed by a doctor
Children 2 under 6 years; of age | ½ tablets every 4 hours,; not to exceed 2 tablets; in 24 hours or as; directed by a doctor
Children under 2; years of age | Consult physician

INACTIVE INGREDIENT

Inactive ingredients: Magnesium Stearate, microcrystalline cellulose, sodium starch glycolate

Other information

- Store at room temperature 59°-86°F (15°-30°C) [see USP Controlled Room Temperature]

Tamper evident by foil seal under cap. Do not use if foil seal is broken or missing

New Formulation

Contains the same active ingredients as Despec® DM Tablets*

• ANTITUSSIVE • EXPECTORANT • NASAL DECONGESTANT

Manufactured in the USA for Kramer Novis. San Juan, PR 00917. www.kramernovis.com / (787) 767-2072

* Despec® DM Tablets is a registered trademark of International Ethical Laboratories. This product is not manufactured, distributed or marketed by International Ethical Laboratories.